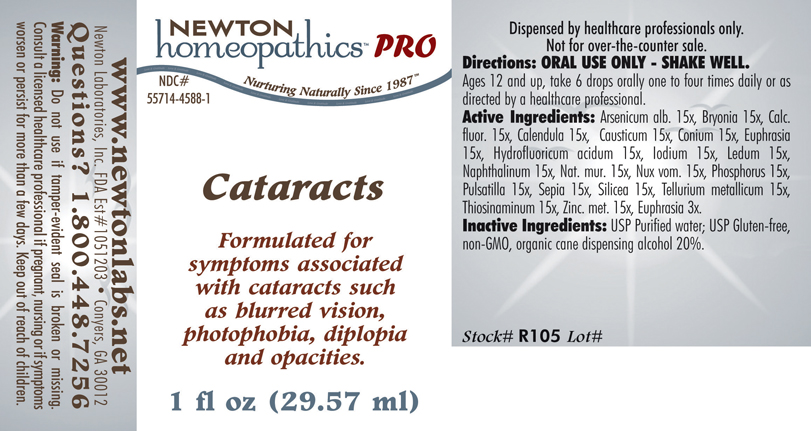 DRUG LABEL: Cataracts 
NDC: 55714-4588 | Form: LIQUID
Manufacturer: Newton Laboratories, Inc.
Category: homeopathic | Type: HUMAN PRESCRIPTION DRUG LABEL
Date: 20110601

ACTIVE INGREDIENTS: Arsenic Trioxide 15 [hp_X]/1 mL; Bryonia Alba Root 15 [hp_X]/1 mL; Calcium Fluoride 15 [hp_X]/1 mL; Calendula Officinalis Flowering Top 15 [hp_X]/1 mL; Causticum 15 [hp_X]/1 mL; Conium Maculatum Flowering Top 15 [hp_X]/1 mL; Euphrasia Stricta 15 [hp_X]/1 mL; Hydrofluoric Acid 15 [hp_X]/1 mL; Iodine 15 [hp_X]/1 mL; Ledum Palustre Twig 15 [hp_X]/1 mL; Naphthalene 15 [hp_X]/1 mL; Sodium Chloride 15 [hp_X]/1 mL; Strychnos Nux-vomica Seed 15 [hp_X]/1 mL; Phosphorus 15 [hp_X]/1 mL; Pulsatilla Vulgaris 15 [hp_X]/1 mL; Sepia Officinalis Juice 15 [hp_X]/1 mL; Silicon Dioxide 15 [hp_X]/1 mL; Tellurium 15 [hp_X]/1 mL; Allylthiourea 15 [hp_X]/1 mL; Zinc 15 [hp_X]/1 mL; Euphrasia Stricta 3 [hp_X]/1 mL
INACTIVE INGREDIENTS: Alcohol

Cataracts

PRODUCT NAME & INDICATIONS SECTION

CATARACTS Formulated for symptoms associated with cataracts such as blurred vision, photophobia, diplopia and opacities.

DIRECTION SECTION

Directions: ORAL USE ONLY - SHAKE WELL. Ages 12 and up, take 6 drops orally one to four times daily or as directed by a healthcare professional.

ACTIVE INGREDIENT SECTION

Arsenicum alb. 15x, Bryonia 15x, Calc. fluor. 15x, Calendula 15x, Causticum 15x, Conium 15x, Euphrasia 15x, Hydrofluoricum acidum 15x, Iodium 15x, Ledum 15x, Naphthalinum 15x, Nat. mur. 15x, Nux vom. 15x, Phosphorus 15x, Pulsatilla 15x, Sepia 15x, Silicea 15x, Tellurium metallicum 15x, Thiosinaminum 15x, Zinc. met. 15x, Euphrasia 3x.

PURPOSE SECTION

Formulated for symptoms associated with cataracts such as blurred vision, photophobia, diplopia and opacities.

INACTIVE INGREDIENT SECTION

Inactive Ingredients: USP Purified Water; USP Gluten-free, non-GMO, organic cane dispensing alcohol 20%.

QUESTIONS? SECTION

www.newtonlabs.net Newton Laboratories, Inc. FDA Est # 1051203 -Conyers, GA 30012
Questions? 1.800.448.7256

WARNINGS SECTION

Warning: Do not use if tamper - evident seal is broken or missing. Consult a licensed healthcare professional if pregnant, nursing or if symptoms worsen or persist for more than a few days. Keep out of reach of children.

OTC - PREGNANCY OR BREAST FEEDING SECTION

Consult a licensed healthcare professional if pregnant or nursing or if symptoms worsen or persist for more than a few days.

OTC - KEEP OUT OF REACH OF CHILDREN SECTION

Keep out of reach of children.